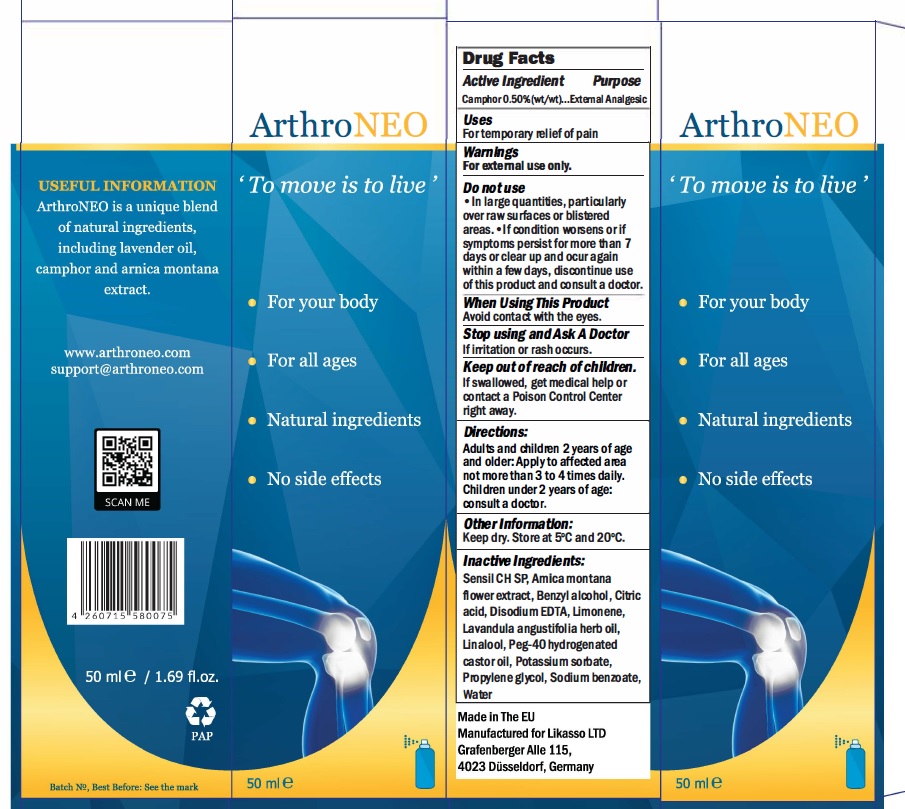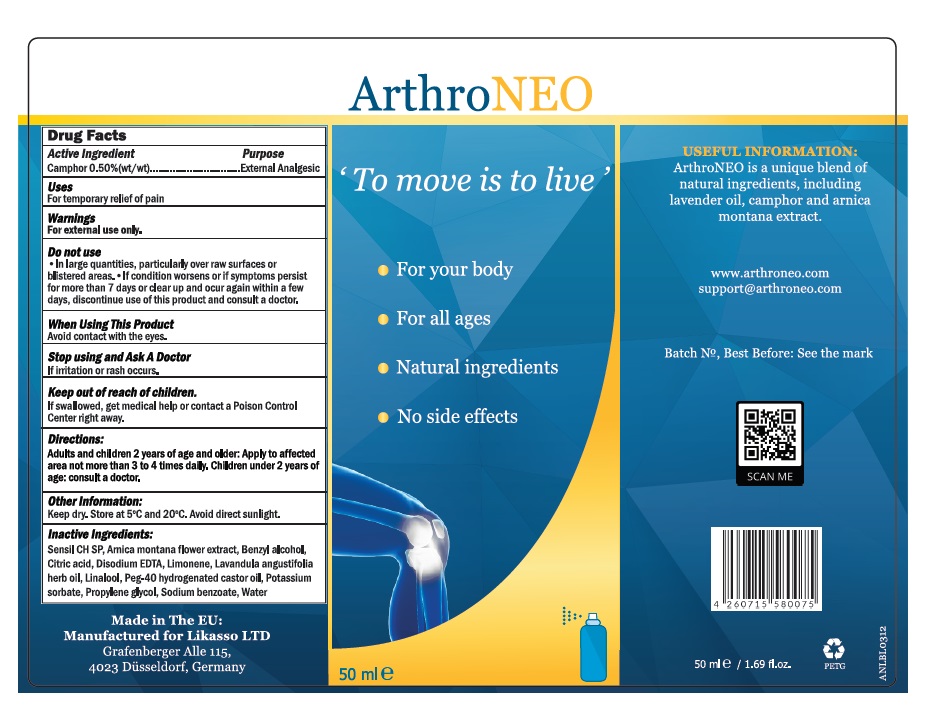 DRUG LABEL: ArthroNEO
NDC: 82225-001 | Form: SPRAY
Manufacturer: Hakimian Global LLC
Category: otc | Type: HUMAN OTC DRUG LABEL
Date: 20211027

ACTIVE INGREDIENTS: CAMPHOR (NATURAL) 0.5 g/100 g
INACTIVE INGREDIENTS: ANHYDROUS CITRIC ACID; ARNICA MONTANA FLOWER; BENZYL ALCOHOL; LAVANDULA ANGUSTIFOLIA FLOWER; LINALOOL, (+)-; SODIUM BENZOATE; WATER; EDETATE DISODIUM; LIMONENE, (+)-; PEG-40 CASTOR OIL; PROPYLENE GLYCOL; POTASSIUM SORBATE

ArthroNEO (Hakimian Global LLC | 82225-001-50)

Active Ingredient

Camphor 0.50%

Purpose

External Analgesic

Uses

For temporary relief of pain

Warnings

For external use only.

Do Not use

In large quantities, particularly over raw surfaces or blistered areas.• If condition worsens or if symptoms persist for more than 7 days or clear up and ocur again within a few days, discontinue use of this product and consult a doctor.

When Using This Product

Avoid contact with the eyes

Stop using and Ask a Doctor

if irritation or rash occurs.

Keep Out Of Reach of Children

If swallowed, get medical help or contact a Poison Control Center right away.

Directions

Adults and children 2 years of age and older: Apply to affected area not more than 3 to 4 times daily. Children under 2 years of age:
consult a doctor.

Other Information

Keep dry. Store at 5'C and 20'C.

Inactive Ingredients

Sensil CH SP, Amica montana flower extract, Benzyl alcohol, Citric acid, Disodium EDTA, Limonene, Lavandula angustifolia herb oil,
Linalool, Peg-40 hydrogenated castor oil, Potassium sorbate, Propylene glycol, Sodium benzoate, Water

Principal Display

Made in the EU

Manufacturered for Likasso, LTD

Grafenberger Alle 115

4023 Dusseldorf, Germany

NDC: 82225-001-50